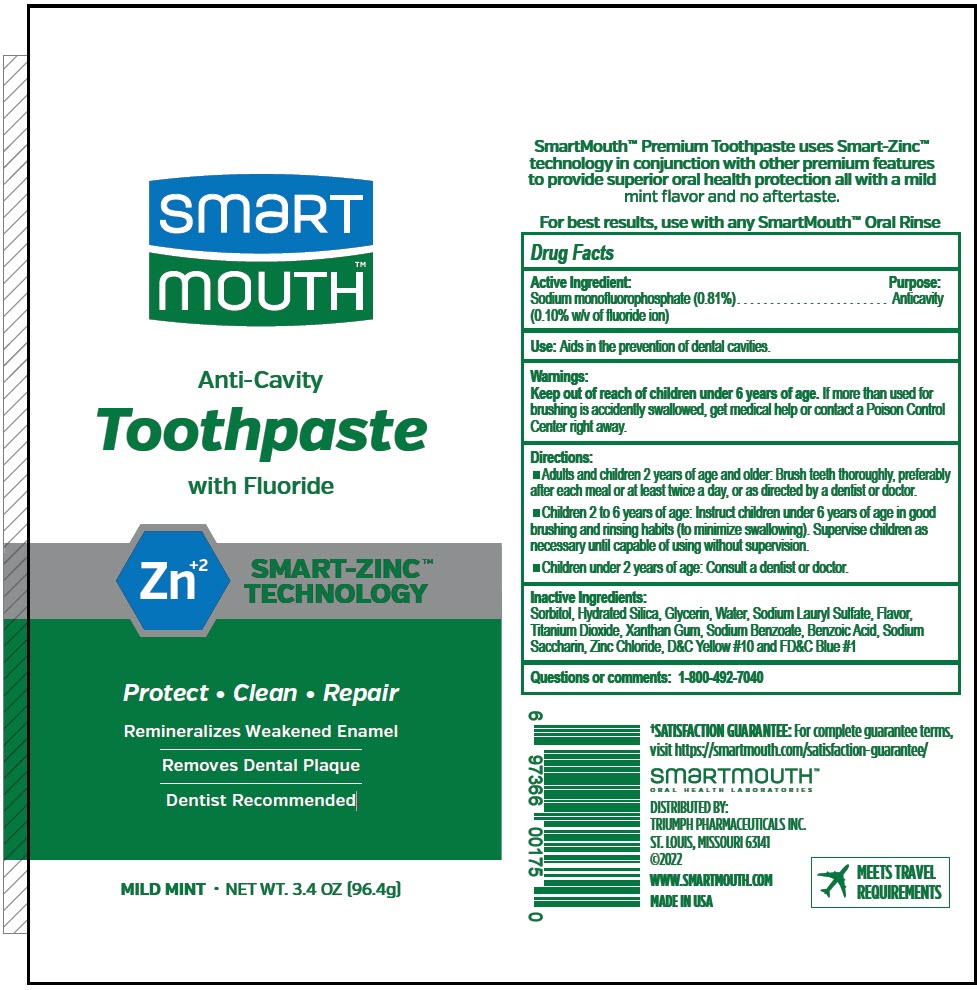 DRUG LABEL: SmartMouth Premium Action
NDC: 76357-175 | Form: PASTE, DENTIFRICE
Manufacturer: Triumph Pharmaceuticals Inc.
Category: otc | Type: HUMAN OTC DRUG LABEL
Date: 20241220

ACTIVE INGREDIENTS: Sodium Monofluorophosphate 10.21 g/96.4 g
INACTIVE INGREDIENTS: Sorbitol; Hydrated Silica; Glycerin; Water; Sodium Lauryl Sulfate; Titanium Dioxide; XANTHAN GUM; Sodium Benzoate; Benzoic Acid; Saccharin Sodium; Zinc Chloride

SmartMouth™ Premium Action Toothpaste
SmartMouth™ Toothpaste Advanced Clinical Formula (ACF)

Drug Facts

Active Ingredient

Sodium monofluorophosphate (0.81%) (0.10% w/v of fluoride ion)

Purpose

Anticavity

Use

Aids in the prevention of dental cavities.

Warnings

Keep out of reach of children under 6 years of age. If more than used for brushing is accidently swallowed, get medical help or contact a Poison Control Center right away.

Directions

- Adults and children 2 years of age and older: Brush teeth thoroughly, preferably after each meal or at least twice a day, or as directed by a dentist or doctor.
- Children 2 to 6 years of age: Instruct children under 6 years of age in good brushing and rinsing habits (to minimize swallowing). Supervise children as necessary until capable of using without supervision.
- Children under 2 years of age: Consult a dentist or doctor.

Inactive Ingredients

Sorbitol, Hydrated Silica, Glycerin, Water, Sodium Lauryl Sulfate, Flavor, Titanium Dioxide, Xanthan Gum, Sodium Benzoate, Benzoic Acid, Sodium Saccharin, Zinc Chloride, D&C Yellow #10 and FD&C Blue #1

Questions or comments

1-800-492-7040

Smartmouth® is a trademark
of and distributed by:
Triumph Pharmaceuticals Inc.
St. Louis, Missouri 63114

PRINCIPAL DISPLAY PANEL - 96.4 g Tube Label

smart
mouth™

Anti-Cavity
Toothpaste
with Fluoride

Zn^+2

SMART-ZINC™
TECHNOLOGY

Protect • Clean • Repair

Remineralizes Weakened Enamel

Removes Dental Plaque

Dentist Recommended

MILD MINT • NET WT. 3.4 OZ (96.4g)